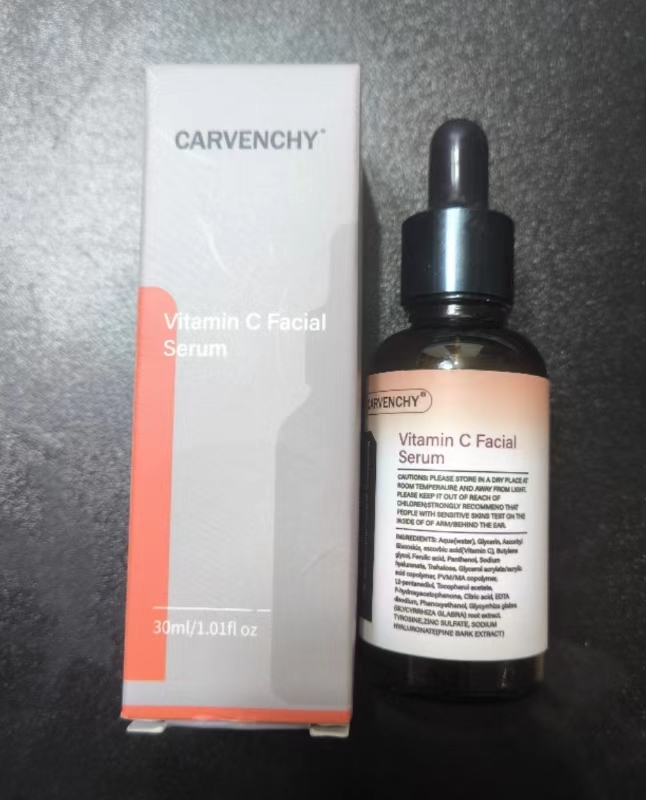 DRUG LABEL: Vitamin C Facial Serum
NDC: 84727-061 | Form: LIQUID
Manufacturer: Guangzhou Baishili Trading Co., Ltd
Category: otc | Type: HUMAN OTC DRUG LABEL
Date: 20240928

ACTIVE INGREDIENTS: 2-O-ETHYL ASCORBIC ACID 1000 mg/5 mL
INACTIVE INGREDIENTS: ASCORBYL GLUCOSIDE 1000 mg/5 mL; BUTYLENE GLYCOL 1000 mg/5 mL; FERULIC ACID 1000 mg/5 mL; PANTHENOL 1000 mg/5 mL; TREHALOSE 1000 mg/5 mL; ZINC SULFATE 1000 mg/5 mL; GLYCERIN 1000 mg/5 mL; PEG-9 DIGLYCIDYL ETHER/SODIUM HYALURONATE CROSSPOLYMER 1000 mg/5 mL; TYROSINE 1000 mg/5 mL; WATER 1000 mg/5 mL; PHENOXYETHANOL 1000 mg/5 mL

Active ingredients

ASCORBIC ACID 10%

Purpose

BRIGHTENING SKIN, MOISTURIZINGFRECKLES REMOVAL AND WHITEN.ING,ANTI-OXIDATION

Uses

Valid BRIGHTENING SKIN, MOISTURIZINGFRECKLES REMOVAL AND WHITEN.ING,ANTI-OXIDATION

CAUTIONS

Please store in a dry place at room temperaure and away from light.

Stop use and ask a doctor if

If you feel uncomfortable, please stop using it.

Do not use

on damaged or broken skin

When using this product

keep out of eyes. Rinse with water to remove.

Keep out of reach of children.

if swallowed, get medical help or contact a Poison Control Center right away.

INACTIVE INGREDIENT

GLYCERIN

ASCORBYL GLUCOSIDE

BUTYLENE GLYCOL

FERULIC ACID

PANTHENOL

SODIUM HYALURONATE

TREHALOSE

TOCOPHEROL ACETATE

P-HYDROXYACETOPHENONE

CITRIC ACID

EDTA DISODIUM

PHENOXYETHANOL

GLYCYRRHIZA GLABRA ROOT EXTRACT

TYROSINE

ZINC SULFATE

SODIUM HYALURONATE

DOSAGE & ADMINISTRATION SECTION

Apply 1 ml to the skin surface each time